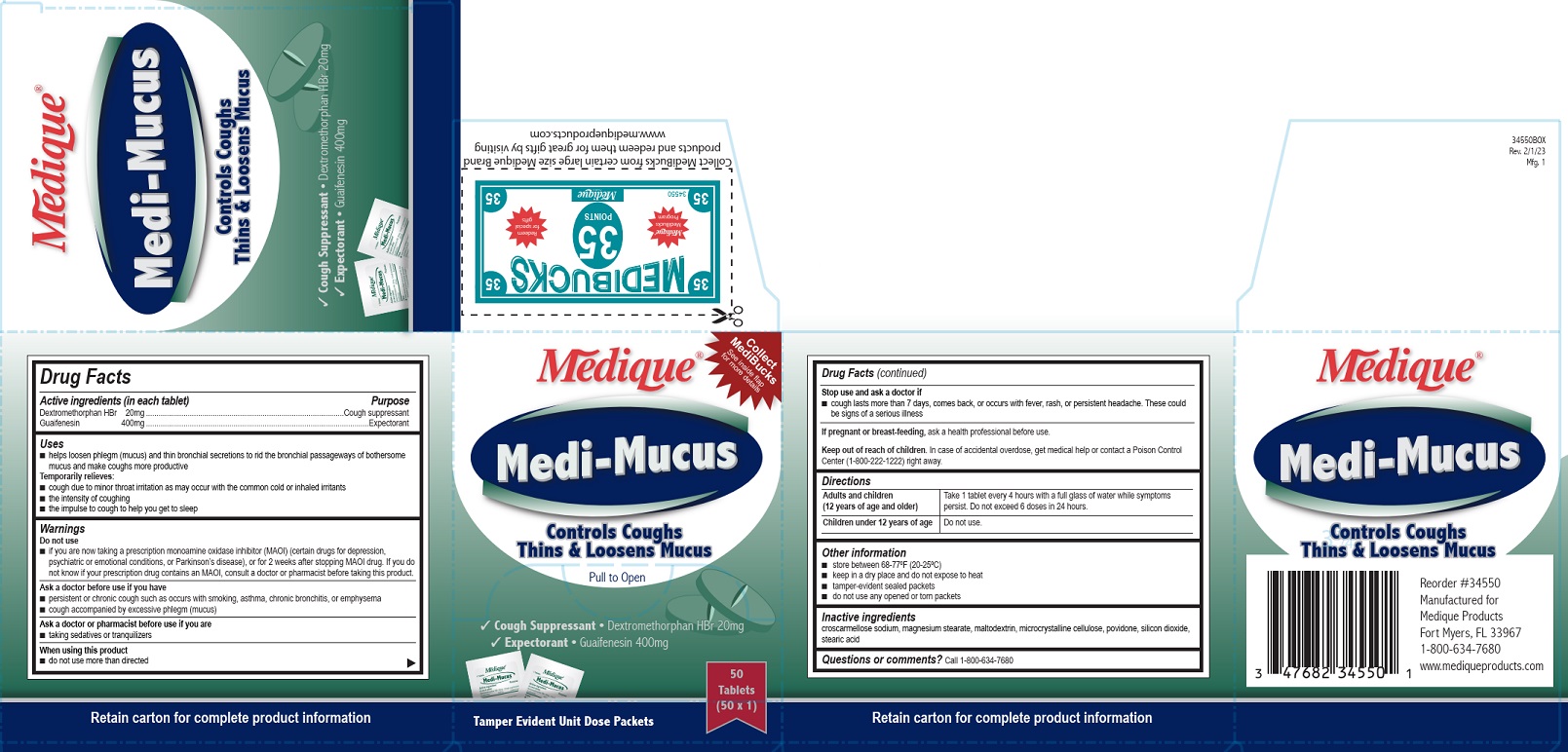 DRUG LABEL: Medique Medi-Mucus
NDC: 47682-432 | Form: TABLET
Manufacturer: Unifirst First Aid Corporation
Category: otc | Type: HUMAN OTC DRUG LABEL
Date: 20250908

ACTIVE INGREDIENTS: DEXTROMETHORPHAN HYDROBROMIDE 20 mg/1 1; GUAIFENESIN 400 mg/1 1
INACTIVE INGREDIENTS: MALTODEXTRIN; POVIDONE; CROSCARMELLOSE SODIUM; SILICON DIOXIDE; CELLULOSE, MICROCRYSTALLINE; MAGNESIUM STEARATE; STEARIC ACID

Medique Medi-Mucus

Drug Facts

Active ingredients (in each tablet)

Dextromethorphan HBr 20 mg

Guaifenesin 400 mg

Purpose

Cough suppressant

Expectorant

Uses

- helps loosen phlegm (mucus) and thin bronchial secretions to rid the bronchial passageways of bothersome mucus and make coughs more productive

Temporarily relieves:

- cough due to minor throat irritations as may occur with the common cold or inhaled irritants
- the intensity of coughing
- the impulse to cough to help you get sleep

Warnings

Do not use

- if you are now taking a prescription monoamine oxidase inhibitor (MAOI) (certain drugs for depression, psychiatric or emotional conditions, or Parkinson's disease), or for 2 weeks after stopping the MAOI drug. If you do not know if your prescription drug contains an MAOI, ask a doctor or pharmacist before taking this product.

Ask a doctor before use if you have

- persistent or chronic cough such as occurs with smoking, asthma, chronic bronchitis or emphysema
- cough that occurs with excessive phlegm (mucus)

Ask a doctor or pharmacist before use if you are

- taking sedatives or tranquilizers

When using this product

- do not use more than directed

Stop use and ask a doctor if

- cough lasts more than 7 days, comes back, or occurs with fever, rash, or persistent headache. These could be signs of a serious illness.

PREGNANCY OR BREAST FEEDING

If pregnant or breast-feeding, ask a health professional before use.

Keep out of reach of children. In case of accidental overdose, get medical help or contact a Poison Control Center (1-800-222-1222) right away.

Directions

Adults and children (12 years of age and older)

Take 1 tablet every 4 hours with a full glass of water while symptoms persist. Do not exceed 6 doses in 24 hours.

Children under 12 years of age

Do not use.

Other information

- store between 68-77ºF (20-25ºC)
- keep in a dry place and do not expose to heat
- tamper-evident sealed packets
- do not use any opened or torn packets

Inactive ingredients

croscarmellose sodium, magnesium stearate, maltodextrin, microcrystalline cellulose, povidone, silicon dioxide, stearic acid

Questions or comments?

Call 1-800-634-7680

PACKAGE LABEL

Medique®

Medi-Mucus

Cough Suppressant • Dextromethorphan HBr 20 mg

Expectorant • Guaifenesin 400 mg

Controls Coughs Thins & Loosens Mucus

Pull to Open

Tamper Evident Unit Dose Packets

Collect MediBuckSee inside flap for more details

50 Tablets (50 x 1)